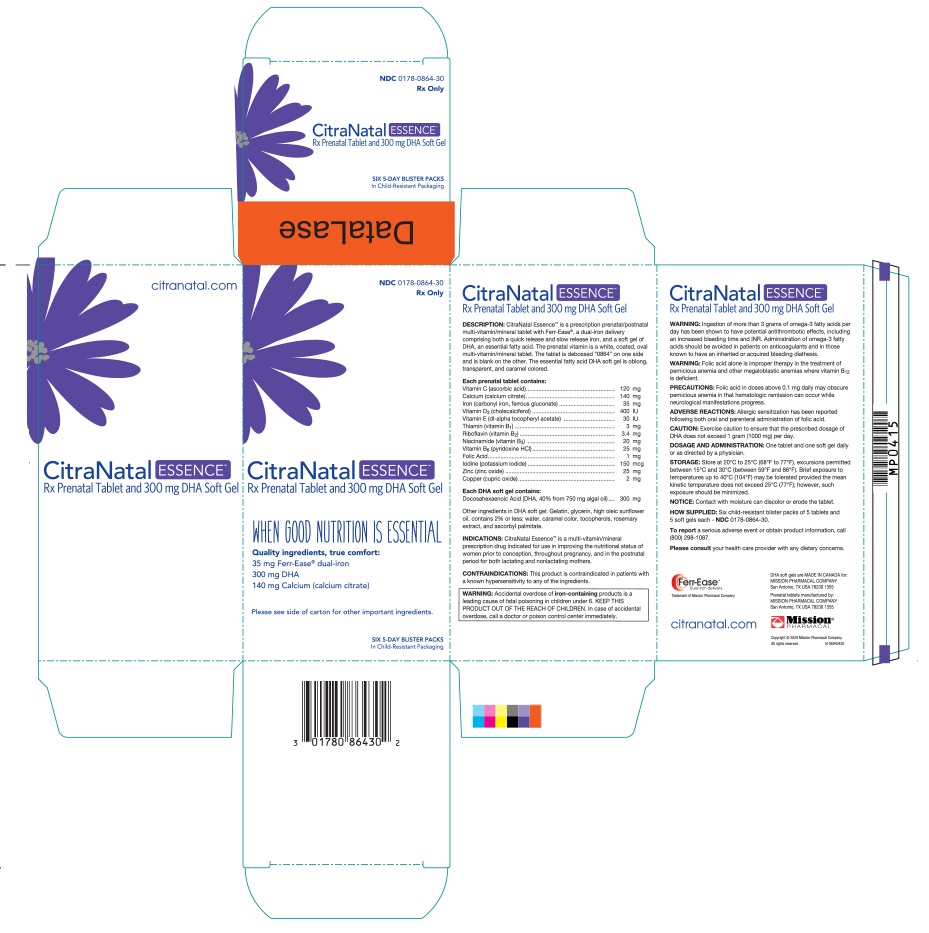 DRUG LABEL: CitraNatal Essence
NDC: 0178-0864 | Form: KIT | Route: ORAL
Manufacturer: Mission Pharmacal Company
Category: prescription | Type: HUMAN PRESCRIPTION DRUG LABEL
Date: 20200707

ACTIVE INGREDIENTS: ASCORBIC ACID 120 mg/1 1; IRON 35 mg/1 1; CHOLECALCIFEROL 400 [iU]/1 1; ALPHA-TOCOPHEROL 30 [iU]/1 1; RIBOFLAVIN 3.4 mg/1 1; NIACINAMIDE 20 mg/1 1; PYRIDOXINE HYDROCHLORIDE 25 mg/1 1; FOLIC ACID 1 mg/1 1; IODINE 150 ug/1 1; ZINC 25 mg/1 1; COPPER 2 mg/1 1; THIAMINE 3 mg/1 1; CALCIUM CITRATE 140 mg/1 1; DOCONEXENT 300 mg/1 1; ICOSAPENT 0.75 mg/1 1
INACTIVE INGREDIENTS: POVIDONE K30; CROSCARMELLOSE SODIUM; TITANIUM DIOXIDE; MAGNESIUM SILICATE; MAGNESIUM STEARATE; SHELLAC; VANILLIN; GELATIN; SUNFLOWER OIL; GLYCERIN; LECITHIN, SUNFLOWER; ROSEMARY; TOCOPHEROL; ASCORBYL PALMITATE

CitraNatal EssenceTM
Rx Prenatal Vitamin Tablet and 300 mg DHA Capsule

DESCRIPTION

CitraNatal Essence™ is a prescription prenatal/postnatal multi-vitamin/ mineral tablet with Ferr-Ease®, a dual-iron delivery comprising both a quick release and slow release iron, and a soft gel of DHA, an essential fatty acid. The prenatal vitamin is a white, coated, oval multi-vitamin/mineral tablet. The tablet is debossed “0864” on one side and is blank on the other. The essential fatty acid DHA soft gel is oblong, transparent, and caramel colored.

INDICATIONS

CitraNatal EssenceTM is a multivitamin/mineral prescription drug indicated for use in improving the nutritional status of women prior to conception, throughout pregnancy, and in the postnatal period for both lactating and nonlactating mothers.

CONTRAINDICATIONS

This product is contraindicated in patients with a known hypersensitivity to any of the ingredients.

WARNING

Accidental overdose of iron-containing products is a leading cause of fatal poisoning in children under 6. KEEP THIS PRODUCT OUT OF THE REACH OF CHILDREN. In case of accidental overdose, call a doctor or poison control center immediately.

WARNING

Ingestion of more than 3 grams of omega-3 fatty acids per day has been shown to have potential antithrombotic effects, including an increased bleeding time and INR. Administration of omega-3 fatty acids should be avoided in patients on anticoagulants and in those known to have an inherited or acquired bleeding diathesis.

WARNING

Folic acid alone is improper therapy in the treatment of pernicious anemia and other megaloblastic anemias where vitamin B12 is deficient.

PRECAUTIONS

Folic acid in doses above 0.1 mg daily may obscure pernicious anemia in that hematologic remission can occur while neurological manifestations progress.

ADVERSE REACTIONS

Allergic sensitization has been reported following both oral and parenteral administration of folic acid.

DOSAGE AND ADMINISTRATION

One tablet and one capsule daily or as directed by a physician.

STORAGE

Store at 20–25°C (68–77°F)

NOTICE

Contact with moisture can discolor or erode the tablet.

To report a serious adverse event or obtain product information, call (210) 696-8400.

51065R0420

Mission®
PHARMACAL

DHA capsules manufactured for:
MISSION PHARMACAL COMPANY
San Antonio, TX USA 78230 1355
Prenatal tablets manufactured by:
MISSION PHARMACAL COMPANY
San Antonio, TX USA 78230 1355

Copyright © 2020 Mission Pharmacal Company.

All rights reserved.

www.missionpharmacal.com

Ferr-Ease®
Dual-iron delivery

Trademark of Mission Pharmacal Company
U.S. Patent No. 6,521,247

life's DHA®

life’sDHA is a trademark of DSM.
U.S. Patent No. 7,579,174
U.S. Patent No. 7,732,170
U.S. Patent No. 5,518,918

*March of Dimes does not endorse
specific products or brands.
March of Dimes is a registered trademark
of the March of Dimes Foundation.

HOW SUPPLIED

Six child-resistant blister packs of 5 tablets and 5 capsules each - NDC 0178-0864-30

PACKAGE LABEL

Retail Carton